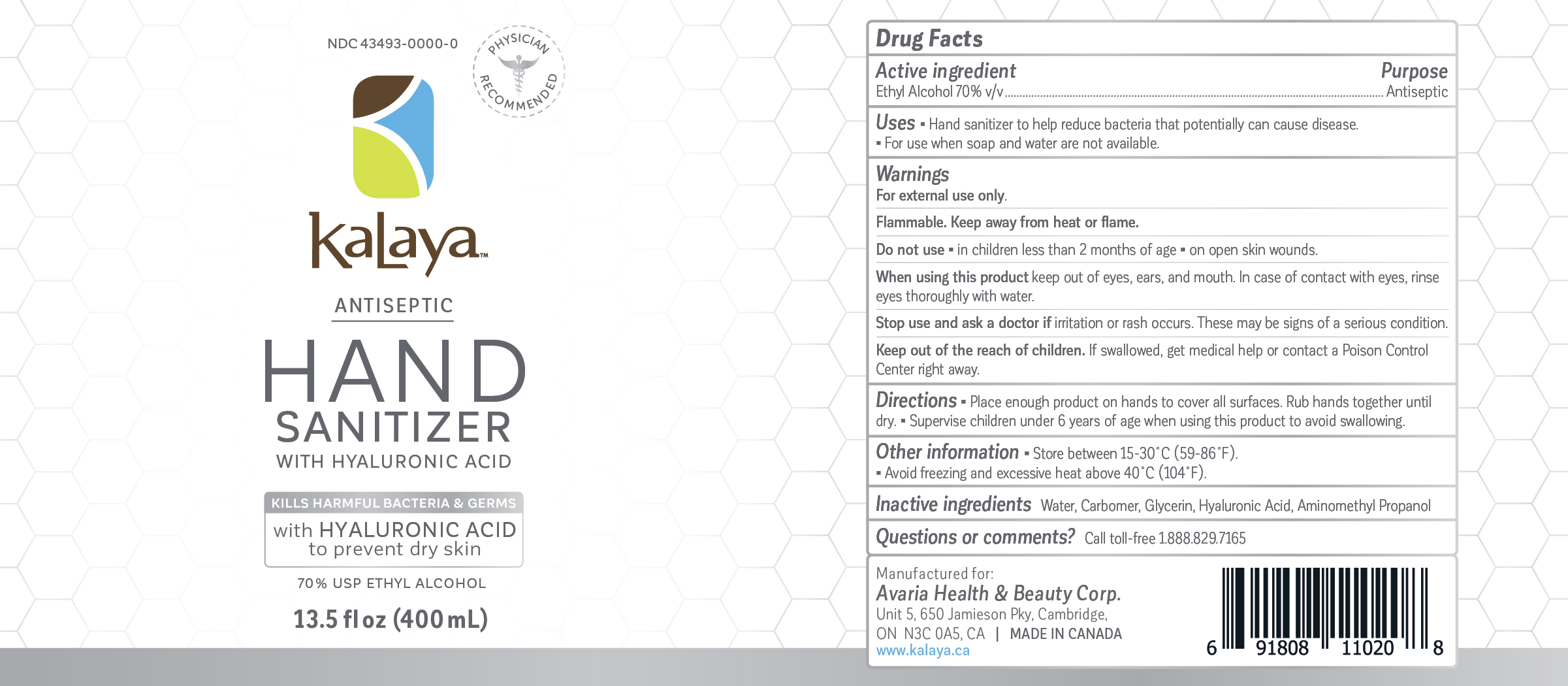 DRUG LABEL: Hand Sanitizer
NDC: 43493-0000 | Form: GEL
Manufacturer: Avaria Health & Beauty Corp
Category: otc | Type: HUMAN OTC DRUG LABEL
Date: 20251008

ACTIVE INGREDIENTS: ALCOHOL 280 mL/400 mL
INACTIVE INGREDIENTS: CARBOMER HOMOPOLYMER, UNSPECIFIED TYPE; ISOPROPYL MYRISTATE; HYALURONIC ACID; WATER; AMINOMETHYLPROPANOL

Kalaya Antiseptic Hand Sanitizer

Active Ingredient(s)

Ethyl Alcohol 70%. Purpose: Antiseptic

Purpose

Antiseptic, Hand Sanitizer

Use

- Hand sanitizer to help reduce bacteria that potentially can cause disease.
- For use when soap and water are not available.

Warnings

For external use only

Flammable. Keep away from heat and flame.

Do not use

- In children less than 2 months of age.
- On open skin wounds.

When using this product

keep out of eyes, ears, and mouth. In case of contact with eyes, rinse eyes thoroughly with water.

Stop use and ask a doctor if

irritation or rash occurs. These may be signs of a serious condition.

Keep out of reach of children. If swallowed, get medical help or contact a Poison Control Center right away.

Directions

- Place enough product on hands to cover all surfaces. Rub hands together until dry.
- Supervise children under 6 years of age when using this product to avoid swallowing.

Other information

- Store between 15 - 40C (59 - 86F)
- Avoid freezing and excessive heat above 40C (104F)

Inactive ingredients

Water, Carbomer, Hyaluronic Acid, Aminomethyl Propanol ,Isopropyl Myristate

Uses

Warnings

Dosage and Administration

Questions or comments?

Call toll-free 1.888.829.7165

Package Label - Principal Display Panel

13.5 fl oz (400 ml)

NDC 43493-0000-0